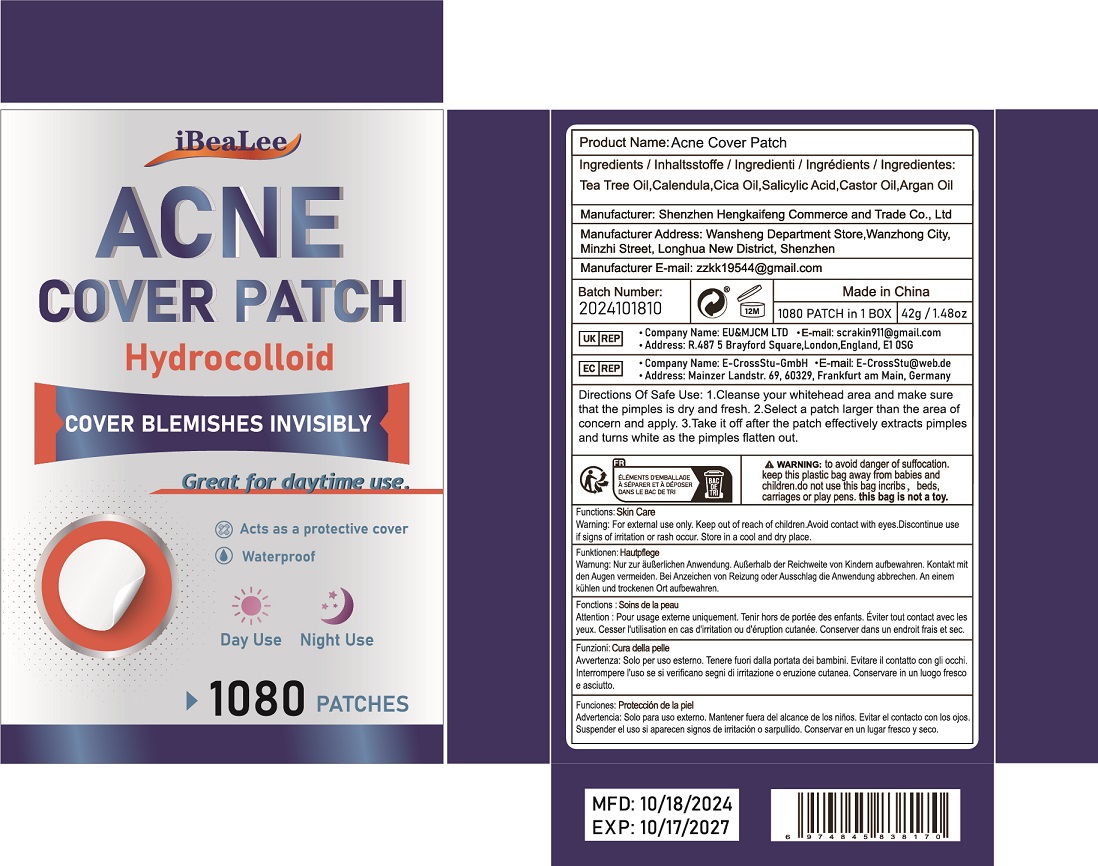 DRUG LABEL: Acne Cover Patch
NDC: 84117-034 | Form: PATCH
Manufacturer: Shenzhen Hengkaifeng Commerce and Trade Co., Ltd
Category: otc | Type: HUMAN OTC DRUG LABEL
Date: 20241018

ACTIVE INGREDIENTS: SALICYLIC ACID 1 g/100 1
INACTIVE INGREDIENTS: WATER

ACTIVE INGREDIENT

Salicylic Acid

Purpose

Acne Treatment

Use

for the treatment of acne

Warnings

For external use only

Do not use this if you have very sensitive skin or if you are sensitive to benzoyl peroxide.

When using this product

keep away from eyes, lips and mouth

wavoid unnecessary sun exposure and use a sunscreen
avoid contact with hair or dyed fabric, including carpet and clothing which may be bleached by this product
skin irritation may occur, characterized by redness, burning, itching, peeling, or possibly
swelling. Mild irritation may be reduced by using the product less frequenty or in a lower concentration.
Ifirritation becomes severe,discontinue use; ifirritation still continues, consulta doctor
wusing other topical acne medication at the same time or immediately following the use of this product may
increase dryness or iritation of the skin, lf this occurs, only one medication should be used unless directed
by a doctor.

Keep out of reach of children.tfswallowed, get help or contact
a Poison Control Center right away.Avoid contact with the eyes. lf contact occurs,flush thoroughly with water.

Directions Of Safe Use:

Cleanse skin thoroughly before appying Acne patch. Cover the enire afected
area with a thin layer 1-3 times daiy. lf bothersome dryness or peeing occurs, reduce application to once a day.

Other information

Keep tightly closed.Avoid storing at extreme temperatures (below 40° fand above 100° F).

Inactive ingredients

Tea Tree Oil,Calendula,Cica Oil,Castor Oil,Argan Oil

DOSAGE & ADMINISTRATION

stick on acne